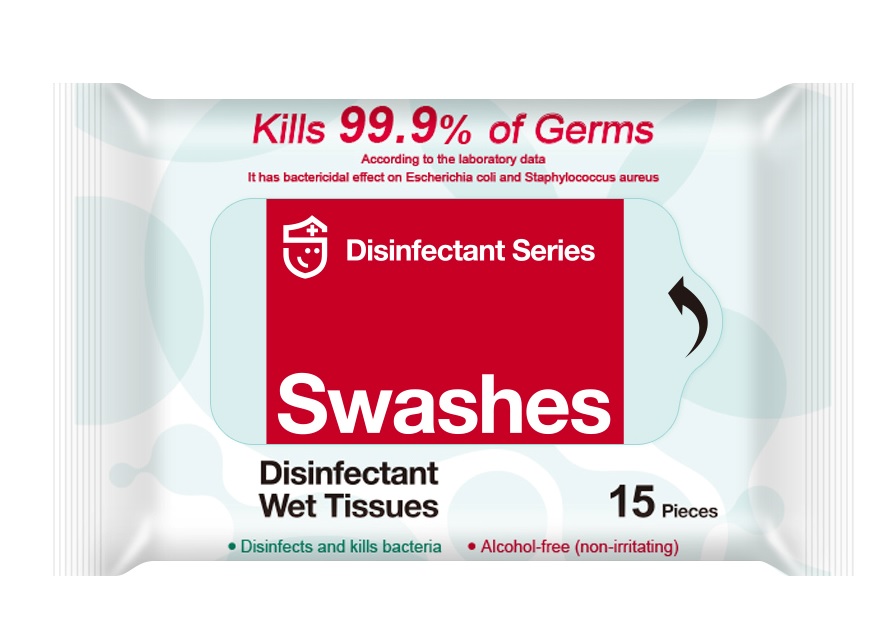 DRUG LABEL: Disinfectant Wet Tissues
NDC: 74974-010 | Form: CLOTH
Manufacturer: Swashes (Shenzhen) Co., Ltd.
Category: otc | Type: HUMAN OTC DRUG LABEL
Date: 20200413

ACTIVE INGREDIENTS: CHLORHEXIDINE ACETATE 0.2 g/100 mL
INACTIVE INGREDIENTS: C12-15 PARETH-10; GLYCERIN; WATER; PEG-10 LANOLIN; METHYLCHLOROISOTHIAZOLINONE; METHYLISOTHIAZOLINONE

Disinfectant Wet Tissues 74974-010

Disinfectant Wet Tissues

Active Ingredient(s)

Chlorhexidine acetate 0.2g/100mL

Purpose: Antiseptic

Purpose

Antiseptic

Use

Disinfectant Wet Tissues to help reduce bacteria that potentially can cause disease. For use when soap and water are not available.

Warnings

For external use only. Flammable. Keep away from heat or flame

Do not use

- in children less than 2 months of age
- on open skin wounds

When using this product keep out of eyes, ears, and mouth. In case of contact with eyes, rinse eyes thoroughly with water.
Stop use and ask a doctor if irritation or rash occurs. These may be signs of a serious condition.
Keep out of reach of children. If swallowed, get medical help or contact a Poison Control Center right away.

Stop use and ask a doctor if irritation or rash occurs. These may be signs of a serious condition.

Keep out of reach of children. If swallowed, get medical help or contact a Poison Control Center right away.

Directions

- Wipe the skin, hands and face for sanitation and disinfection
- Supervise children under 6 years of age when using this product to avoid swallowing.

Other information

- Store between 15-30C (59-86F)
- Avoid freezing and excessive heat above 40C (104F)

Inactive ingredients

Primary Alcobol Ethoxylate
Medicinal Glycerin
Ethoxylated lanolin
Kathon.cmit/mit
Purity Water

Package Label - Principal Display Panel

15 CLOTH IN 1 PACKAGE NDC: 74974-010-01